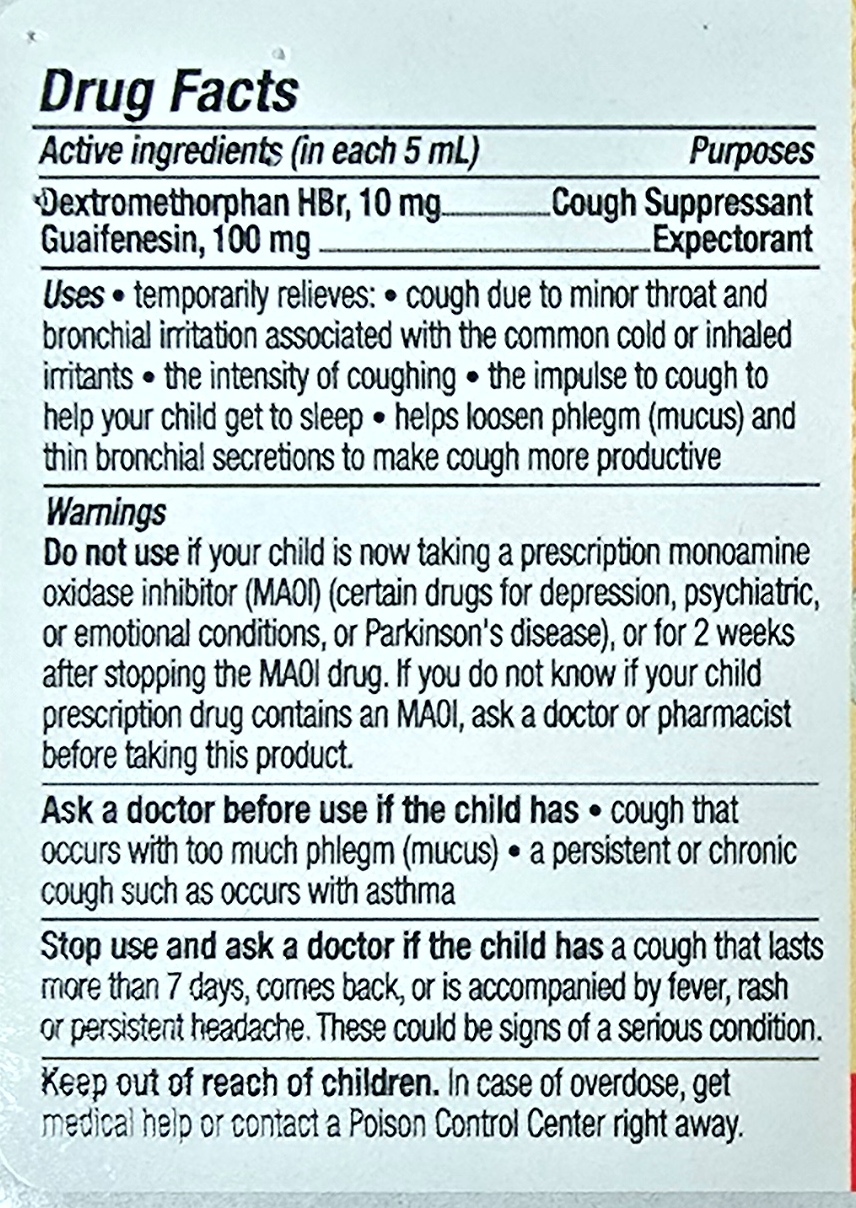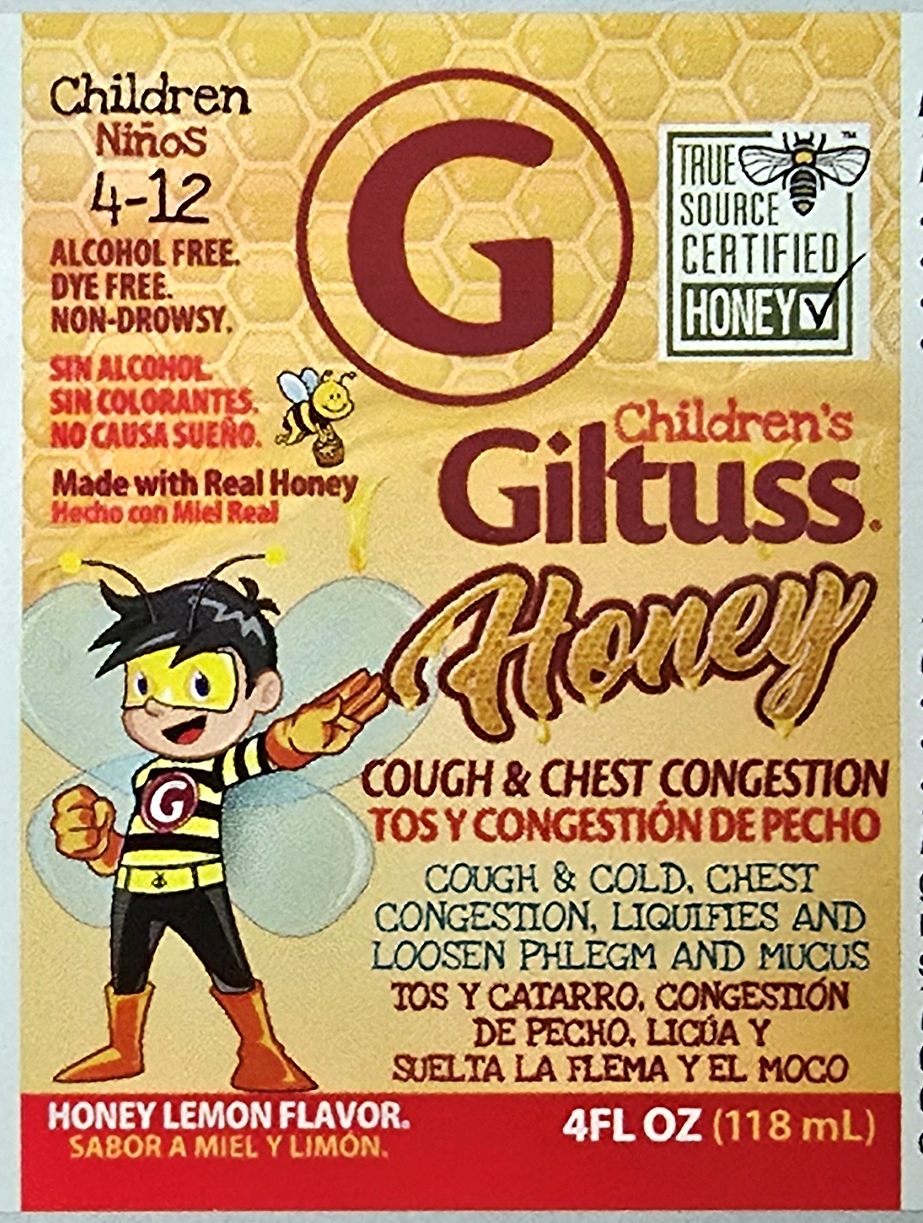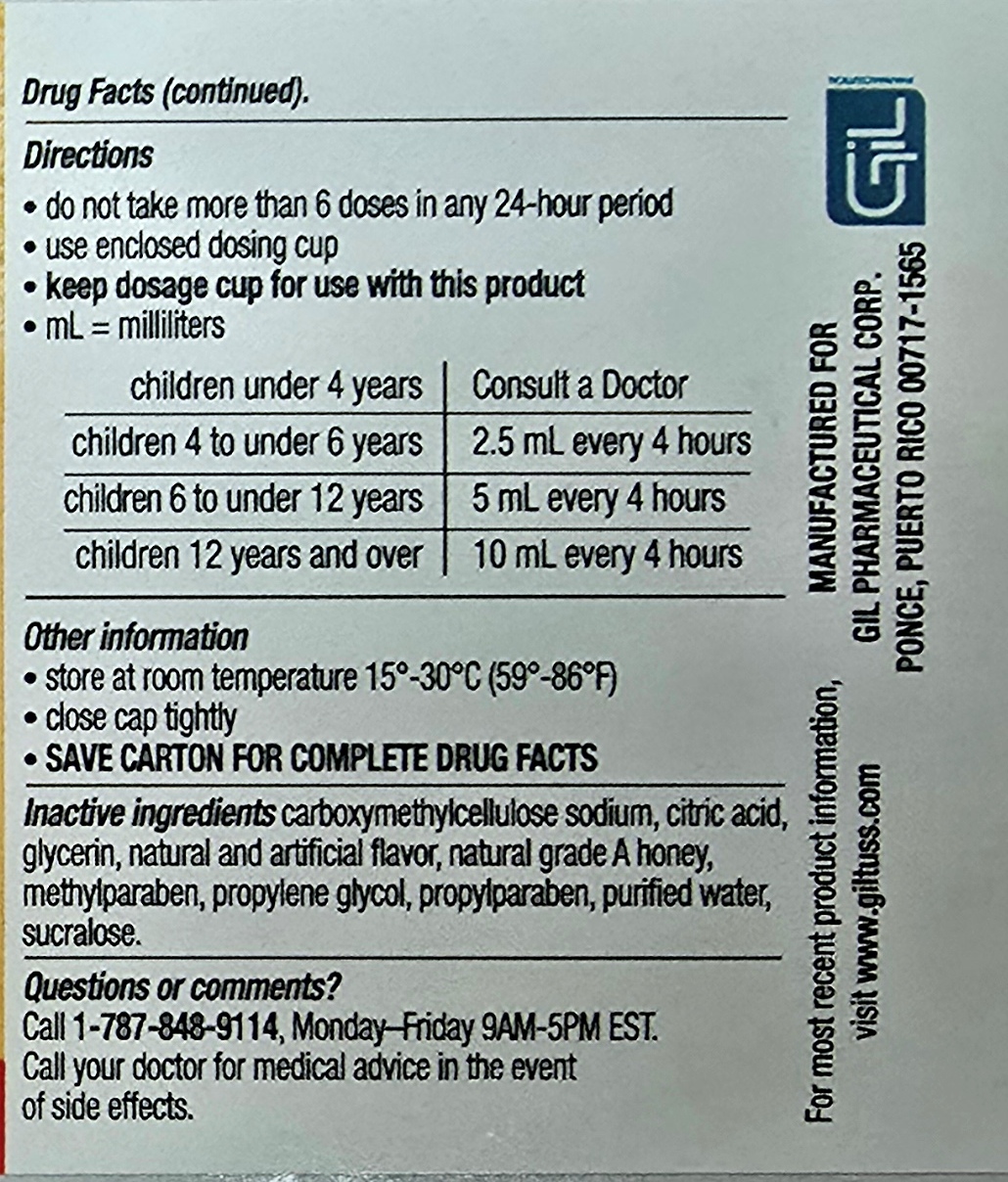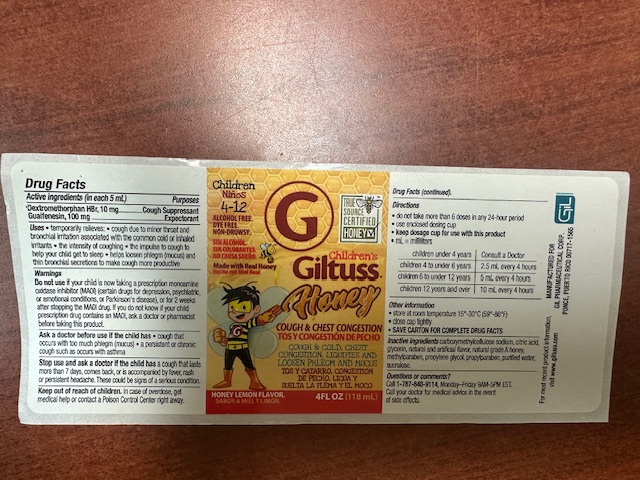 DRUG LABEL: Childrens Giltuss Honey Cough and Chest Congestion
NDC: 65852-003 | Form: SOLUTION
Manufacturer: Dextrum Laboratories, Inc
Category: otc | Type: HUMAN OTC DRUG LABEL
Date: 20250924

ACTIVE INGREDIENTS: DEXTROMETHORPHAN HYDROBROMIDE 10 mg/5 mL; GUAIFENESIN 100 mg/5 mL
INACTIVE INGREDIENTS: CITRIC ACID; PROPYLENE GLYCOL; WATER; HONEY; PROPYLPARABEN; SUCRALOSE; CARBOXYMETHYLCELLULOSE SODIUM; GLYCERIN; METHYLPARABEN

Children's Giltuss Honey Cough & Chest Congestion

Active Ingredients

Active Ingredients (in Each 5 ml) Purposes

Dextromethorphan HBr, 10 mg ------------------------Cough Suppresant

Guaifenesin, 100 mg --------------------------------------Expectorant

Uses

Uses

Temporary relieves:

Cough due to minor throat and bronchial irritation associated with the common cold or inhaled irritants, the intensity of coughing , the impulse to cough to help your child get to sleep, helps loosen phlegm (mucus) and thin bronchial secretions to make cough more productive

warnings

Do not use

If your child is now taking a prescription monoamine oxidase inhibitor (MAOI) (certain drugs for depression, psychiatric, or emotional conditions, or Parkinson's disease), or for 2 weeks after stopping the MAOI drug. If you don’t know is your prescription drug contains and MAOI, ask a doctor or pharmacist before taking this product.

Ask a doctor before use if the child has

Warnings

Ask a doctor before use if your child has, cough that occurs with too much phlegm (mucus) , a persistent or chronic cough as occurs with asthma.

Stop use

Stop use and ask a doctor if

cough lasts for more than 7 days , come back, or is accompanied by fever, rash or persistent headache. These could be signs of serious condition.

Keep out of reach of children. In case of accidental overdose, get medical or professional help or contact a Poisson Control center immediately

Directions

Do not take more than 6 doses in any 24 hours period

use enclosed dosing cup

Keep dosage cup for use with this product

ml= milliliters

children under 4 years of age Consult a doctor

children 4 to under 6 years of age 2.5 ml every 4 hours

children 6 to under 12 years of age 5 ml every 4 hours

Adults and children 12 years & over 10 ml every 4 hours

Other information

Store at room temperature 15-30 °C (59° -86 ° F)
Close cap tightly
SAVE CARTON FOR COMPLETE DRUG FACTS

Inactive ingredients

Carboxymethylcellulose sodium, citric acid, glycerin, natural and artificial flavor, natural grade A honey, methylparaben, propylene glycol, propylparaben, purified water,sucralose

Questions or comments?

Call 1-787-848-9114, Monday-Friday 9AM – 5PM EST

Call your doctor for medical advice in the event of side effects.

Indication and usage section

Do not take more than 6 doses in any 24 hours period

use enclosed dosing cup

Keep dosage cup for use with this product

ml= milliliters

children under 4 years of age Consult a doctor

children 4 to under 6 years of age 2.5 ml every 4 hours

children 6 to under 12 years of age 5 ml every 4 hours

Adults and children 12 years & over 10 ml every 4 hours

PACKAGE LABEL

Children 4-12

Alcohol free, Dye free, Non-drowsy

True source certified honey

Children's Giltuss Honey

Cough & Chest Congestion

Cough & cold, chest congestion, liquifies and loosen phlegm and mucus

Honey lemon flavor

4 floz 118 ml